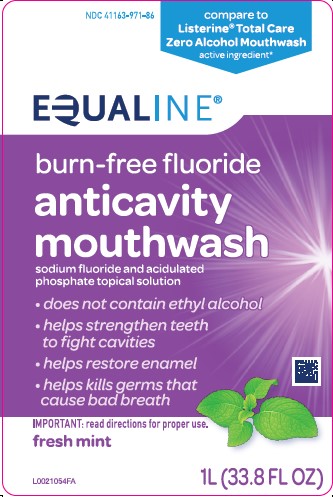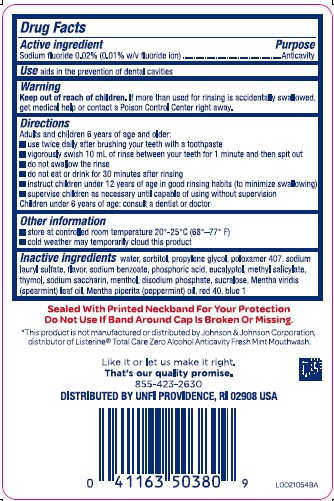 DRUG LABEL: Anticavity
NDC: 41163-971 | Form: RINSE
Manufacturer: United Natural Foods, Inc. dba UNFI
Category: otc | Type: HUMAN OTC DRUG LABEL
Date: 20260217

ACTIVE INGREDIENTS: SODIUM FLUORIDE 0.1 mg/1 mL
INACTIVE INGREDIENTS: WATER; SORBITOL; PROPYLENE GLYCOL; POLOXAMER 407; SODIUM LAURYL SULFATE; SODIUM BENZOATE; PHOSPHORIC ACID; EUCALYPTOL; METHYL SALICYLATE; THYMOL; SACCHARIN SODIUM; MENTHOL, UNSPECIFIED FORM; SODIUM PHOSPHATE, DIBASIC, ANHYDROUS; SUCRALOSE; SPEARMINT OIL; PEPPERMINT OIL; FD&C RED NO. 40; FD&C BLUE NO. 1

Equaline 971.001/971AB
Anticavity Fluoride Rinse

Active Ingredient

Sodium fluoride 0.02% (0.01% w/v fluoride ion)

Purpose

Anticavity

Use

aids in the prevention of dental cavities

Warning

for this product

Keep out of Reach of Children

If more than used for rinsing is accidentally swallowed, get medical help or contact a Poison Control Center right away.

Directions

Adults and children 6 years of age and older:

- use twice daily after brushing your teeth with a toothpaste
- vigorously swish 10 mL of rinse between your teeth for 1 minute and then spit out
- do not swallow the rinse
- do not eat or drink for 30 minutes after rinsing
- instruct children under 12 years of age in good rinsing habits (to minimize swallowing)
- supervise children as necessary until capable of using without supervision

Children under 6 years of age: consult a dentist or doctor

Other information

- store at controlled room temperature 20⁰ - 25⁰C (68⁰ - 77⁰F)
- cold weather may temporarily cloud this product

Inactive ingredients

water, sorbitol, propylene glycol, poloxamer 407, sodium lauryl sulfate, flavor, sodium benzoate, phosphoric acid, eucalyptol, methyl salicylate, thymol, sodium saccharin, menthol, disodium phosphate, sucralose, Mentha viridis (spearmint) leaf oil, Mentha piperita (peppermint) oil, red 40, blue 1

Tamper Evident Statement

Sealed With Printed Neckband For Your Portection

Do Not Use If Band Around Cap Is Broken or Missing.

Disclaimer

*This product is not manufactured or distributed by Johnson & Johnson Corporation, distributer or Listerine®Total Care Zero Alcohol Anticavity Fresh Mint Mouthwash.

Like it or let us make it right.

That's our quality promise.

855-423-2630

DISTRIBUTED BY UNFI PROVIDENCE, RI 02908 USA

Principal panel display

NDC 41163-971-86

compare to Listerine®Total Care Zero Alcohol Mouthwash active ingredient*

EQUALINE®

burn-free fluoride

anti-cavity

mouthwash

Sodium Fluoride and Acidulated Phosphate Topical Solution

- does not contain ethyl alcohol
- helps strengthen teeth to fight cavities
- helps restore enamel
- kills germs that couse bad breath

IMPORTANT: read directions for proper use.

FRESH MINT

1 L (33.8 FL OZ)